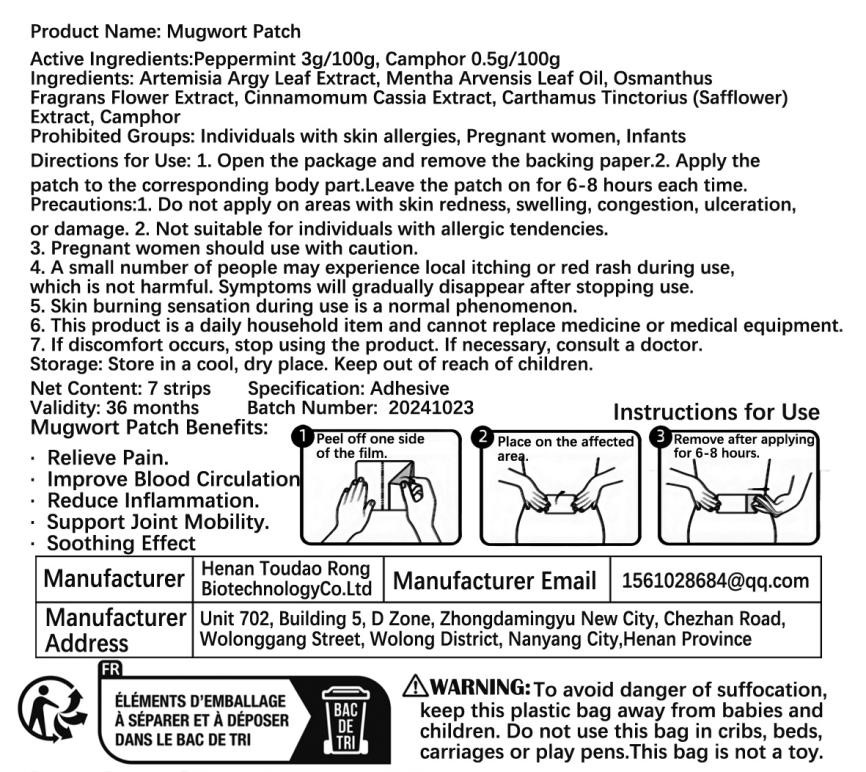 DRUG LABEL: Mugwort
NDC: 85136-001 | Form: PATCH
Manufacturer: Henan Toudaorong Biotechnology Co., Ltd.
Category: otc | Type: HUMAN OTC DRUG LABEL
Date: 20250119

ACTIVE INGREDIENTS: PEPPERMINT 3 g/100 g; CAMPHOR (NATURAL) 0.5 g/100 g
INACTIVE INGREDIENTS: CINNAMON OIL; SAFFLOWER; ARTEMISIA PRINCEPS LEAF; CURCUMA LONGA LEAF

Active ingredients (Strength)

Peppermint 3g/100g Camphor 0.5g/100g

Inactive ingredients

Mugwort Leaf Extract, Peppermint Leaf Oil, Curcuma longa, Cinnamon Extract,Safflower Extract, Camphor

Purpose

Promote blood circulation

Relieve muscle soreness

Soothe joint discomfort

Relieve cold and dampness

OTC - keep out of reach of children section

Adults only.

Indications & usage section

Indications for Use:

· Relieve Pain.

· Improve Blood Circulation

· Reduce Inflammation.

· Support Joint Mobility.

· Soothing Effect

Warnings section

lf symptoms persist, please consult your healthcare professionals. Non-GMO/Gluten Free.This product cannot replace medicine. Allergens, pregnant women, and children are prohibited from using it.

Dosage & administration section

1. Do not apply on areas with skin redness, swelling, congestion, ulceration, or damage.

2. Not suitable for individuals with allergic tendencies.

3. Pregnant women, and children are prohibited from using it.

4. A small number of people may experience local itching or red rash during use, which is not harmful. Symptoms will gradually disappear after stopping use.

5. Skin burning sensation during use is a normal phenomenon.

6. This product is a daily household item and cannot replace medicine or medical equipment.

If discomfort occurs, stop using the product. If necessary, consult a doctor.

STOP USE

lf symptoms persist, please consult your healthcare professionals. Non-GMO/Gluten Free.This product cannot replace medicine. Allergens, pregnant women, and children are prohibited from using it.

when

1. Do not apply on areas with skin redness, swelling, congestion, ulceration, or damage.

2. Not suitable for individuals with allergic tendencies.

3. Pregnant women, and children are prohibited from using it.

4. A small number of people may experience local itching or red rash during use, which is not harmful. Symptoms will gradually disappear after stopping use.

5. Skin burning sensation during use is a normal phenomenon.

6. This product is a daily household item and cannot replace medicine or medical equipment.

If discomfort occurs, stop using the product. If necessary, consult a doctor.